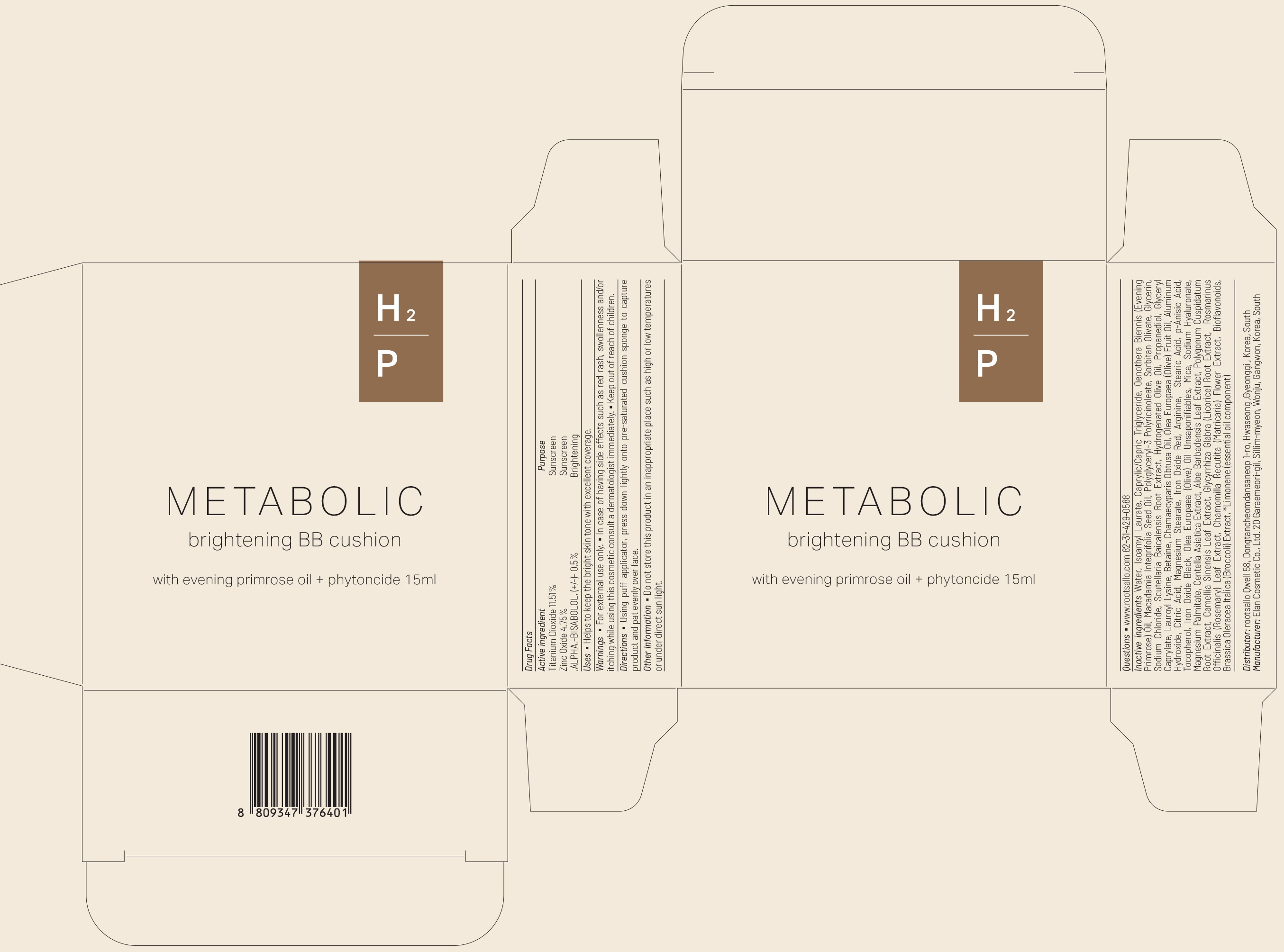 DRUG LABEL: METABOLIC BRIGHTENING BB CUSHION
NDC: 82450-010 | Form: POWDER
Manufacturer: rootsallo Qwell
Category: otc | Type: HUMAN OTC DRUG LABEL
Date: 20211230

ACTIVE INGREDIENTS: Titanium Dioxide 11.51 g/100 mL; Zinc Oxide 4.75 g/100 mL; .ALPHA.-BISABOLOL, (+/-)- 0.5 g/100 mL
INACTIVE INGREDIENTS: Water; Isoamyl Laurate; MEDIUM-CHAIN TRIGLYCERIDES

ACTIVE INGREDIENTS

Titanium Dioxide 11.51%
Zinc Oxide 4.75%
.ALPHA.-BISABOLOL, (+/-)- 0.5%

PURPOSE

Sunscreen, Brightening

Uses

Helps to keep the bright skin tone with excellent coverage.

Warnings

For external use only.
In case of having side effects such as red rash, swollenness and/or itching while using this cosmetic consult a dermatologist immediately.
Keep out of reach of children.

KEEP OUT OF REACH OF CHILDREN

Directions

Using puff applicator, press down lightly onto pre-saturated cushion sponge to capture product and pat evenly over face.

Other Information

Do not store this product in an inappropriate place such as high or low temperatures or under direct sun light.

Questions

www.rootsallo.com 82-31-429-0588

Inactive ingredients

Water, Isoamyl Laurate, Caprylic/Capric Triglyceride, Oenothera Biennis (Evening Primrose) Oil, Macadamia Integrifolia Seed Oil, Polyglyceryl-3 Polyricinoleate, Sorbitan Olivate, Glycerin, Sodium Chloride, Scutellaria Baicalensis Root Extract, Hydrogenated Olive Oil, Propanediol, Glyceryl Caprylate, Lauroyl Lysine, Betaine, Chamaecyparis Obtusa Oil, Olea Europaea (Olive) Fruit Oil, Aluminum Hydroxide, Citric Acid, Magnesium Stearate, Iron Oxide Red, Arginine, Stearic Acid, p-Anisic Acid, Tocopherol, Iron Oxide Black, Olea Europaea (Olive) Oil Unsaponifiables, Mica, Sodium Hyaluronate, Magnesium Palmitate, Centella Asiatica Extract, Aloe Barbadensis Leaf Extract, Polygonum Cuspidatum Root Extract, Camellia Sinensis Leaf Extract, Glycyrrhiza Glabra (Licorice) Root Extract, Rosmarinus Officinalis (Rosemary) Leaf Extract, Chamomilla Recutita (Matricaria) Flower Extract, Bioflavonoids, Brassica Oleracea Italica (Broccoli) Extract, *Limonene (essential oil component)